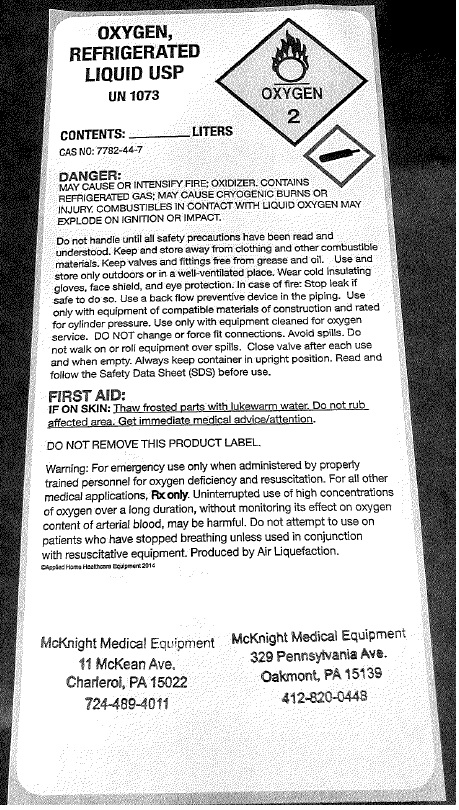 DRUG LABEL: OXYGEN
NDC: 58276-015 | Form: GAS
Manufacturer: Pieri Inc dba McKnight Medical Equipment
Category: prescription | Type: HUMAN PRESCRIPTION DRUG LABEL
Date: 20251024

ACTIVE INGREDIENTS: OXYGEN 99 L/100 L

OXYGEN REFRIGERATED LIQUID USP

OXYGEN

REFRIGERATED

LIQUID USP

UN1073

CONTENTS_________ LITERS

CAS NO: 7782-44-7

DANGER:

MAY CAUSE OR INTENSIFY FIRE: OXIDIZER. CONTAINS

REFRIGERATED GAS; MAYCAUSE CRYOGENIC BURNS OR

INJURY. COMBUSTIBLES IN CONTACT WITH LIQUID OXYGEN MAY

EXPLODE ON IGNITION OR IMPACT.

McKnight Medical Equipment McKnight Medical Equipment

11 McKean Ave. 328 Pennsylvania Ave.

Charlerol, PA 15022 Oakmont, PA 15139

724-489-4011 412-820-0448

res